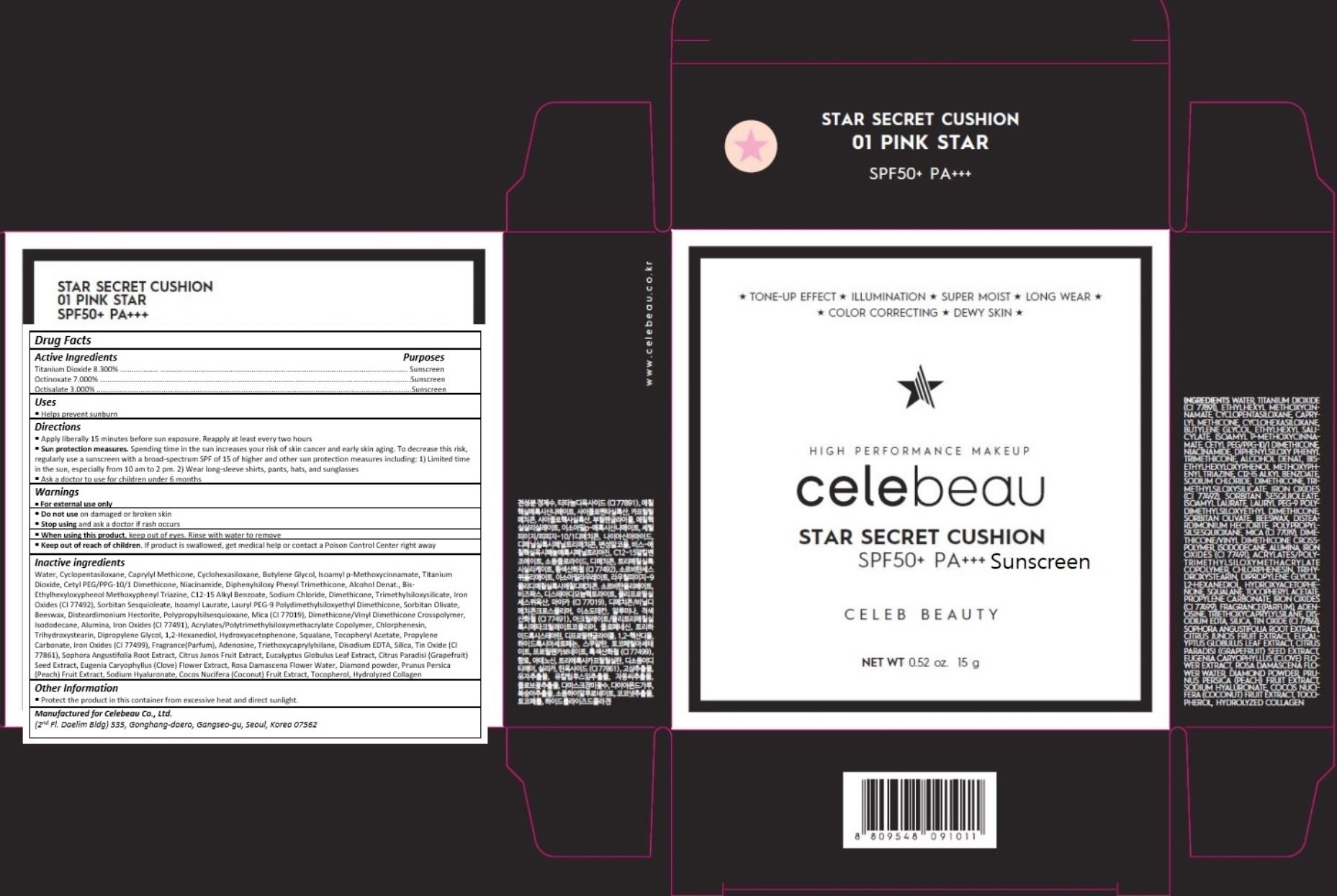 DRUG LABEL: Celebeau Star Secret Cushion 01 Pink Star
NDC: 70142-003 | Form: CREAM
Manufacturer: SD BIOTECHNOLOGIES CO., LTD
Category: otc | Type: HUMAN OTC DRUG LABEL
Date: 20180328

ACTIVE INGREDIENTS: TITANIUM DIOXIDE 1.245 g/15 g; OCTINOXATE 1.05 g/15 g; OCTISALATE 0.45 g/15 g
INACTIVE INGREDIENTS: Water; CYCLOMETHICONE 5; CYCLOMETHICONE 6; CAPRYLYL TRISILOXANE; BUTYLENE GLYCOL; AMILOXATE; CETYL PEG/PPG-10/1 DIMETHICONE (HLB 2); Niacinamide; DIPHENYLSILOXY PHENYL TRIMETHICONE; ALCOHOL; BEMOTRIZINOL; ALKYL (C12-15) BENZOATE; SODIUM CHLORIDE; Dimethicone; TRIMETHYLSILOXYSILICATE (M/Q 0.6-0.8); FERRIC OXIDE YELLOW; SORBITAN SESQUIOLEATE; ISOAMYL LAURATE; LAURYL PEG-9 POLYDIMETHYLSILOXYETHYL DIMETHICONE; SORBITAN OLIVATE; YELLOW WAX; DISTEARDIMONIUM HECTORITE; MICA; DIMETHICONE/VINYL DIMETHICONE CROSSPOLYMER (HARD PARTICLE); Isododecane; ALUMINUM OXIDE; FERROSOFERRIC OXIDE; CHLORPHENESIN; TRIHYDROXYSTEARIN; DIPROPYLENE GLYCOL; 1,2-Hexanediol; HYDROXYACETOPHENONE; SQUALANE; .ALPHA.-TOCOPHEROL ACETATE; PROPYLENE CARBONATE

ACTIVE INGREDIENT

Titanium Dioxide 8.300%

Octinoxate 7.000%

Octisalate 3.000%

PURPOSE

Sunscreen

INDICATIONS AND USAGE

Helps prevent sunburn

DOSAGE AND ADMINISTRATION

Apply liberally 15 minutes before sun exposure. Reapply at least every two hours
Sun protection measures. Spending time in the sun increases your risk of skin cancer and early skin aging. To decrease this risk, regularly use a sunscreen with a broad spectrum SPF of 15 of higher and other sun protection measures including: 1) Limited time in the sun, especially from 10 am to 2 pm. 2) Wear long-sleeve shirts, pants, hats, and sunglasses
Ask a doctor to use for children under 6 months

WARNINGS

For external use only

Do not use on damaged or broken skin

When using this product, keep out of eyes. Rinse with water to remove.

Stop using and ask a doctor if rash occurs.

KEEP OUT OF REACH OF CHILDREN

Keep out of reach of the children. If product is swallowed, get medical help or contact a poison control center right away.

INACTIVE INGREDIENT

Water, Cyclopentasiloxane, Caprylyl Methicone, Cyclohexasiloxane, Butylene Glycol, Isoamyl p-Methoxycinnamate, Titanium Dioxide, Cetyl PEG/PPG-10/1 Dimethicone, Niacinamide, Diphenylsiloxy Phenyl Trimethicone, Alcohol Denat., Bis-Ethylhexyloxyphenol Methoxyphenyl Triazine, C12-15 Alkyl Benzoate, Sodium Chloride, Dimethicone, Trimethylsiloxysilicate, Iron Oxides (CI 77492), Sorbitan Sesquioleate, Isoamyl Laurate, Lauryl PEG-9 Polydimethylsiloxyethyl Dimethicone, Sorbitan Olivate, Beeswax, Disteardimonium Hectorite, Polypropylsilsesquioxane, Mica (CI 77019), Dimethicone/Vinyl Dimethicone Crosspolymer, Isododecane, Alumina, Iron Oxides (CI 77491), Acrylates/Polytrimethylsiloxymethacrylate Copolymer, Chlorphenesin, Trihydroxystearin, Dipropylene Glycol, 1,2-Hexanediol, Hydroxyacetophenone, Squalane, Tocopheryl Acetate, Propylene Carbonate, Iron Oxides (CI 77499), Fragrance(Parfum), Adenosine, Triethoxycaprylylsilane, Disodium EDTA, Silica, Tin Oxide (CI 77861), Sophora Angustifolia Root Extract, Citrus Junos Fruit Extract, Eucalyptus Globulus Leaf Extract, Citrus Paradisi (Grapefruit) Seed Extract, Eugenia Caryophyllus (Clove) Flower Extract, Rosa Damascena Flower Water, Diamond powder, Prunus Persica (Peach) Fruit Extract, Sodium Hyaluronate, Cocos Nucifera (Coconut) Fruit Extract, Tocopherol, Hydrolyzed Collagen

OTHER SAFETY INFORMATION

Protect the product in the container from excessive heat and direct sun